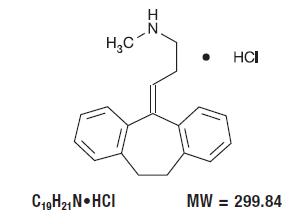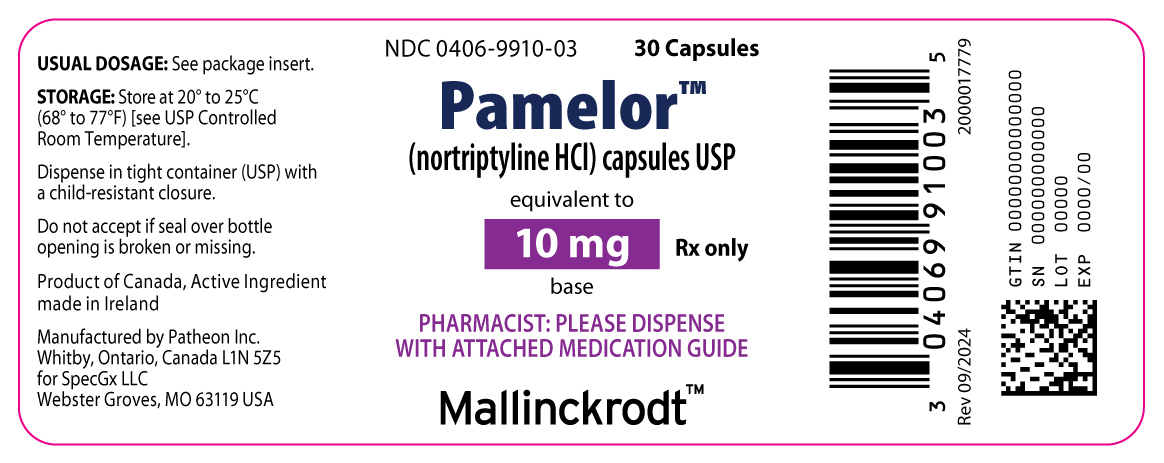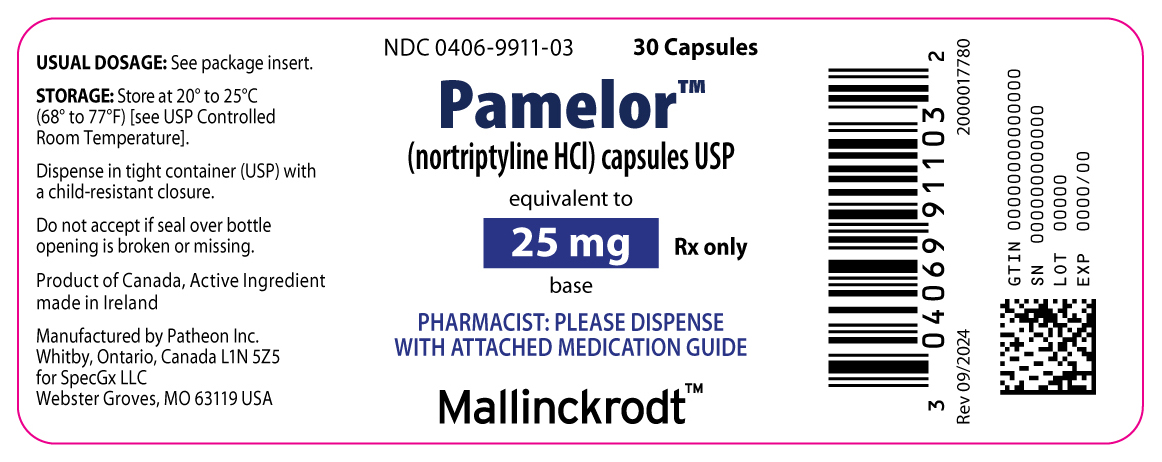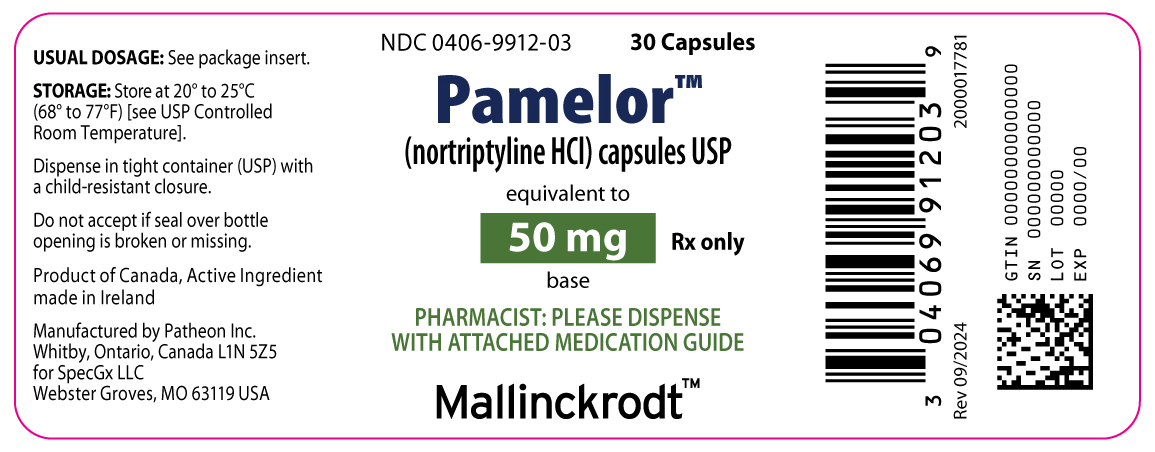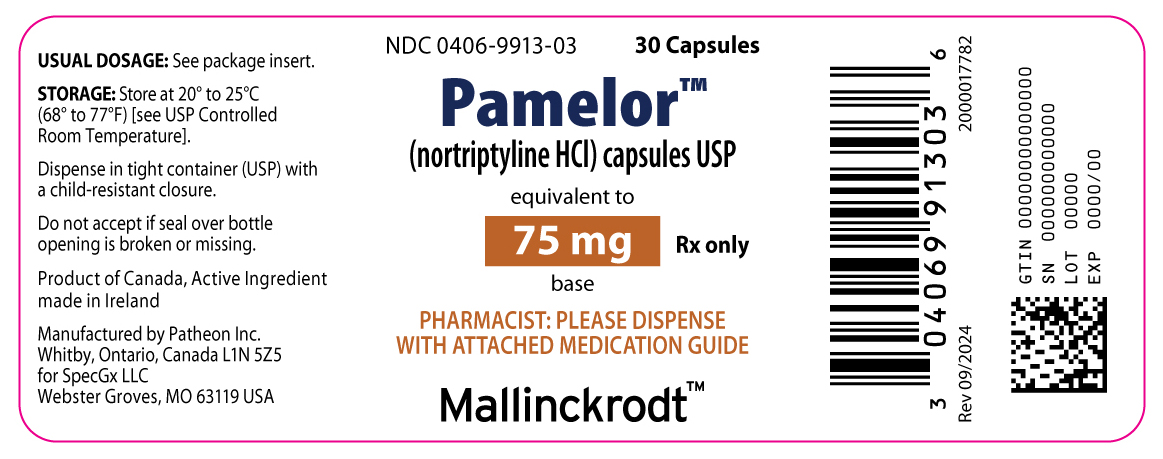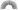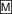 DRUG LABEL: PAMELOR
NDC: 0406-9910 | Form: CAPSULE
Manufacturer: SpecGx LLC
Category: prescription | Type: HUMAN PRESCRIPTION DRUG LABEL
Date: 20241204

ACTIVE INGREDIENTS: NORTRIPTYLINE HYDROCHLORIDE 10 mg/1 1
INACTIVE INGREDIENTS: D&C YELLOW NO. 10; FD&C YELLOW NO. 6; GELATIN, UNSPECIFIED; DIMETHICONE 350; STARCH, CORN; TITANIUM DIOXIDE

Pamelor™
(nortriptyline HCl) capsules USP
Rx only

BOXED WARNING

Suicidality and Antidepressant Drugs
Antidepressants increased the risk compared to placebo of suicidal thinking and behavior (suicidality) in children, adolescents, and young adults in short-term studies of major depressive disorder (MDD) and other psychiatric disorders. Anyone considering the use of nortriptyline hydrochloride or any other antidepressant in a child, adolescent, or young adult must balance this risk with the clinical need. Short-term studies did not show an increase in the risk of suicidality with antidepressants compared to placebo in adults beyond age 24; there was a reduction in risk with antidepressants compared to placebo in adults aged 65 and older. Depression and certain other psychiatric disorders are themselves associated with increases in the risk of suicide. Patients of all ages who are started on antidepressant therapy should be monitored appropriately and observed closely for clinical worsening, suicidality, or unusual changes in behavior. Families and caregivers should be advised of the need for close observation and communication with the prescriber. Nortriptyline hydrochloride is not approved for use in pediatric patients (see WARNINGS, Clinical Worsening and Suicide Risk; PRECAUTIONS, Information for Patients; and PRECAUTIONS, Pediatric Use).

DESCRIPTION

Pamelor™ (nortriptyline HCl) is 1-propanamine, 3-(10,11-dihydro-5H-dibenzo[a,d] cyclohepten-5-ylidene)-N-methyl-, hydrochloride.

The structural formula is as follows:

10 mg, 25 mg, 50 mg, and 75 mg Capsules

Active Ingredient: nortriptyline hydrochloride USP.

10 mg, 25 mg, and 75 mg Capsules

Inactive Ingredients: D&C Yellow #10, FD&C Yellow #6, gelatin, silicone fluid, starch, and titanium dioxide.

50 mg Capsules

Inactive Ingredients: gelatin, silicone fluid, starch, and titanium dioxide.

CLINICAL PHARMACOLOGY

The mechanism of mood elevation by tricyclic antidepressants is at present unknown. Pamelor is not a monoamine oxidase inhibitor. It inhibits the activity of such diverse agents as histamine, 5-hydroxytryptamine, and acetylcholine. It increases the pressor effect of norepinephrine but blocks the pressor response of phenethylamine. Studies suggest that Pamelor interferes with the transport, release, and storage of catecholamines. Operant conditioning techniques in rats and pigeons suggest that Pamelor has a combination of stimulant and depressant properties.

INDICATIONS AND USAGE

Pamelor™ (nortriptyline HCl) is indicated for the relief of symptoms of depression. Endogenous depressions are more likely to be alleviated than are other depressive states.

CONTRAINDICATIONS

Monoamine Oxidase Inhibitors (MAOIs)

The use of MAOIs intended to treat psychiatric disorders with Pamelor or within 14 days of stopping treatment with Pamelor is contraindicated because of an increased risk of serotonin syndrome. The use of Pamelor within 14 days of stopping an MAOI intended to treat psychiatric disorders is also contraindicated (see WARNINGS and DOSAGE AND ADMINISTRATION).

Starting Pamelor in a patient who is being treated with MAOIs such as linezolid or intravenous methylene blue is also contraindicated because of an increased risk of serotonin syndrome (see WARNINGS and DOSAGE AND ADMINISTRATION).

Hypersensitivity to Tricyclic Antidepressants

Cross-sensitivity between Pamelor and other dibenzazepines is a possibility.

Myocardial Infarction

Pamelor is contraindicated during the acute recovery period after myocardial infarction.

WARNINGS

Clinical Worsening and Suicide Risk

Patients with major depressive disorder (MDD), both adult and pediatric, may experience worsening of their depression and/or the emergence of suicidal ideation and behavior (suicidality) or unusual changes in behavior, whether or not they are taking antidepressant medications, and this risk may persist until significant remission occurs. Suicide is a known risk of depression and certain other psychiatric disorders, and these disorders themselves are the strongest predictors of suicide. There has been a long-standing concern, however, that antidepressants may have a role in inducing worsening of depression and the emergence of suicidality in certain patients during the early phases of treatment. Pooled analyses of short-term placebo-controlled trials of antidepressant drugs (SSRIs and others) showed that these drugs increase the risk of suicidal thinking and behavior (suicidality) in children, adolescents, and young adults (ages 18 to 24) with major depressive disorder (MDD) and other psychiatric disorders. Short-term studies did not show an increase in the risk of suicidality with antidepressants compared to placebo in adults beyond age 24; there was a reduction with antidepressants compared to placebo in adults aged 65 and older.

The pooled analyses of placebo-controlled trials in children and adolescents with MDD, obsessive compulsive disorder (OCD), or other psychiatric disorders included a total of 24 short-term trials of 9 antidepressant drugs in over 4400 patients. The pooled analyses of placebo-controlled trials in adults with MDD or other psychiatric disorders included a total of 295 short-term trials (median duration of 2 months) of 11 antidepressant drugs in over 77,000 patients. There was considerable variation in risk of suicidality among drugs, but a tendency toward an increase in the younger patients for almost all drugs studied. There were differences in absolute risk of suicidality across the different indications, with the highest incidence in MDD. The risk differences (drug vs. placebo), however, were relatively stable within age strata and across indications. These risk differences (drug-placebo difference in the number of cases of suicidality per 1000 patients treated) are provided in Table 1.

Table 1
Age Range | Drug-Placebo Difference in Number of Cases of Suicidality per 1000 Patients Treated
Increases Compared to Placebo
<18 | 14 additional cases
18-24 | 5 additional cases
Decreases Compared to Placebo
25-64 | 1 fewer case
≥65 | 6 fewer cases

No suicides occurred in any of the pediatric trials. There were suicides in the adult trials, but the number was not sufficient to reach any conclusion about drug effect on suicide.

It is unknown whether the suicidality risk extends to longer-term use, i.e., beyond several months. However, there is substantial evidence from placebo-controlled maintenance trials in adults with depression that the use of antidepressants can delay the recurrence of depression.

All patients being treated with antidepressants for any indication should be monitored appropriately and observed closely for clinical worsening, suicidality, and unusual changes in behavior, especially during the initial few months of a course of drug therapy, or at times of dose changes, either increases or decreases.

The following symptoms, anxiety, agitation, panic attacks, insomnia, irritability, hostility, aggressiveness, impulsivity, akathisia (psychomotor restlessness), hypomania, and mania, have been reported in adult and pediatric patients being treated with antidepressants for major depressive disorder as well as for other indications, both psychiatric and nonpsychiatric. Although a causal link between the emergence of such symptoms and either the worsening of depression and/or the emergence of suicidal impulses has not been established, there is concern that such symptoms may represent precursors to emerging suicidality.

Consideration should be given to changing the therapeutic regimen, including possibly discontinuing the medication, in patients whose depression is persistently worse, or who are experiencing emergent suicidality or symptoms that might be precursors to worsening depression or suicidality, especially if these symptoms are severe, abrupt in onset, or were not part of the patient's presenting symptoms.

Families and caregivers of patients being treated with antidepressants for major depressive disorder or other indications, both psychiatric and nonpsychiatric, should be alerted about the need to monitor patients for the emergence of agitation, irritability, unusual changes in behavior, and the other symptoms described above, as well as the emergence of suicidality, and to report such symptoms immediately to health care providers. Such monitoring should include daily observation by families and caregivers. Prescriptions for nortriptyline hydrochloride should be written for the smallest quantity of capsules consistent with good patient management, in order to reduce the risk of overdose.

Screening Patients for Bipolar Disorder – A major depressive episode may be the initial presentation of bipolar disorder. It is generally believed (though not established in controlled trials) that treating such an episode with an antidepressant alone may increase the likelihood of precipitation of a mixed/manic episode in patients at risk for bipolar disorder. Whether any of the symptoms described above represent such a conversion is unknown. However, prior to initiating treatment with an antidepressant, patients with depressive symptoms should be adequately screened to determine if they are at risk for bipolar disorder; such screening should include a detailed psychiatric history, including a family history of suicide, bipolar disorder, and depression. It should be noted that nortriptyline hydrochloride is not approved for use in treating bipolar depression.

Patients with cardiovascular disease should be given Pamelor only under close supervision because of the tendency of the drug to produce sinus tachycardia and to prolong the conduction time. Myocardial infarction, arrhythmia, and strokes have occurred. The antihypertensive action of guanethidine and similar agents may be blocked. Because of its anticholinergic activity, Pamelor should be used with great caution in patients who have a history of urinary retention. Patients with a history of seizures should be followed closely when Pamelor is administered, inasmuch as this drug is known to lower the convulsive threshold. Great care is required if Pamelor is given to hyperthyroid patients or to those receiving thyroid medication, since cardiac arrhythmias may develop.

Pamelor may impair the mental and/or physical abilities required for the performance of hazardous tasks, such as operating machinery or driving a car; therefore, the patient should be warned accordingly.

Excessive consumption of alcohol in combination with nortriptyline therapy may have a potentiating effect, which may lead to the danger of increased suicidal attempts or overdosage, especially in patients with histories of emotional disturbances or suicidal ideation.

The concomitant administration of quinidine and nortriptyline may result in a significantly longer plasma half-life, higher AUC, and lower clearance of nortriptyline.

Serotonin Syndrome

The development of a potentially life-threatening serotonin syndrome has been reported with SNRIs and SSRIs, including Pamelor, alone but particularly with concomitant use of other serotonergic drugs (including triptans, tricyclic antidepressants, fentanyl, lithium, tramadol, tryptophan, buspirone, and St. John’s Wort) and with drugs that impair metabolism of serotonin (in particular, MAOIs, both those intended to treat psychiatric disorders and also others, such as linezolid and intravenous methylene blue).

Serotonin syndrome symptoms may include mental status changes (e.g., agitation, hallucinations, delirium, and coma), autonomic instability (e.g., tachycardia, labile blood pressure, dizziness, diaphoresis, flushing, hyperthermia), neuromuscular changes (e.g., tremor, rigidity, myoclonus, hyperreflexia, incoordination), seizures, and/or gastrointestinal symptoms (e.g., nausea, vomiting, diarrhea). Patients should be monitored for the emergence of serotonin syndrome.

The concomitant use of Pamelor with MAOIs intended to treat psychiatric disorders is contraindicated. Pamelor should also not be started in a patient who is being treated with MAOIs such as linezolid or intravenous methylene blue. All reports with methylene blue that provided information on the route of administration involved intravenous administration in the dose range of 1 mg/kg to 8 mg/kg. No reports involved the administration of methylene blue by other routes (such as oral tablets or local tissue injection) or at lower doses. There may be circumstances when it is necessary to initiate treatment with an MAOI such as linezolid or intravenous methylene blue in a patient taking Pamelor. Pamelor should be discontinued before initiating treatment with the MAOI (see CONTRAINDICATIONS and DOSAGE AND ADMINISTRATION).

If concomitant use of Pamelor with other serotonergic drugs, including triptans, tricyclic antidepressants, fentanyl, lithium, tramadol, buspirone, tryptophan, and St. John’s Wort is clinically warranted, patients should be made aware of a potential increased risk for serotonin syndrome, particularly during treatment initiation and dose increases.

Treatment with Pamelor and any concomitant serotonergic agents should be discontinued immediately if the above events occur and supportive symptomatic treatment should be initiated.

Unmasking of Brugada Syndrome

There have been postmarketing reports of an association between treatment with Pamelor and the unmasking of Brugada syndrome. Brugada syndrome is a disorder characterized by syncope, abnormal electrocardiographic (ECG) findings, and a risk of sudden death. Pamelor should generally be avoided in patients with Brugada syndrome or those suspected of having Brugada syndrome.

Angle-Closure Glaucoma

The pupillary dilation that occurs following use of many antidepressant drugs including Pamelor may trigger an angle-closure attack in a patient with anatomically narrow angles who does not have a patent iridectomy.

Use in Pregnancy

Safe use of Pamelor during pregnancy and lactation has not been established; therefore, when the drug is administered to pregnant patients, nursing mothers, or women of childbearing potential, the potential benefits must be weighed against the possible hazards. Animal reproduction studies have yielded inconclusive results.

PRECAUTIONS

Information for Patients

Prescribers or other health professionals should inform patients, their families, and their caregivers about the benefits and risks associated with treatment with nortriptyline hydrochloride and should counsel them in its appropriate use. A patient Medication Guide about “Antidepressant Medicines, Depression and other Serious Mental Illness, and Suicidal Thoughts or Actions” is available for nortriptyline hydrochloride. The prescriber or health professional should instruct patients, their families, and their caregivers to read the Medication Guide and should assist them in understanding its contents. Patients should be given the opportunity to discuss the contents of the Medication Guide and to obtain answers to any questions they may have. The complete text of the Medication Guide is reprinted at the end of this document.

Patients should be advised of the following issues and asked to alert their prescriber if these occur while taking nortriptyline hydrochloride.

Clinical Worsening and Suicide Risk – Patients, their families, and their caregivers should be encouraged to be alert to the emergence of anxiety, agitation, panic attacks, insomnia, irritability, hostility, aggressiveness, impulsivity, akathisia (psychomotor restlessness), hypomania, mania, other unusual changes in behavior, worsening of depression, and suicidal ideation, especially early during antidepressant treatment and when the dose is adjusted up or down. Families and caregivers of patients should be advised to look for the emergence of such symptoms on a day-to-day basis, since changes may be abrupt. Such symptoms should be reported to the patient's prescriber or health professional, especially if they are severe, abrupt in onset, or were not part of the patient's presenting symptoms. Symptoms such as these may be associated with an increased risk for suicidal thinking and behavior and indicate a need for very close monitoring and possibly changes in the medication.

The use of Pamelor in schizophrenic patients may result in an exacerbation of the psychosis or may activate latent schizophrenic symptoms. If the drug is given to overactive or agitated patients, increased anxiety and agitation may occur. In manic-depressive patients, Pamelor may cause symptoms of the manic phase to emerge.

Troublesome patient hostility may be aroused by the use of Pamelor. Epileptiform seizures may accompany its administration, as is true of other drugs of its class.

When it is essential, the drug may be administered with electroconvulsive therapy, although the hazards may be increased. Discontinue the drug for several days, if possible, prior to elective surgery.

The possibility of a suicidal attempt by a depressed patient remains after the initiation of treatment; in this regard, it is important that the least possible quantity of drug be dispensed at any given time.

Both elevation and lowering of blood sugar levels have been reported.

Patients should be advised that taking Pamelor can cause mild pupillary dilation, which in susceptible individuals, can lead to an episode of angle-closure glaucoma. Pre-existing glaucoma is almost always open-angle glaucoma because angle-closure glaucoma, when diagnosed, can be treated definitively with iridectomy. Open-angle glaucoma is not a risk factor for angle-closure glaucoma. Patients may wish to be examined to determine whether they are susceptible to angle closure, and have a prophylactic procedure (e.g., iridectomy), if they are susceptible.

Drug Interactions

Administration of reserpine during therapy with a tricyclic antidepressant has been shown to produce a “stimulating” effect in some depressed patients.

Close supervision and careful adjustment of the dosage are required when Pamelor is used with other anticholinergic drugs and sympathomimetic drugs.

Concurrent administration of cimetidine and tricyclic antidepressants can produce clinically significant increases in the plasma concentrations of the tricyclic antidepressant. The patient should be informed that the response to alcohol may be exaggerated.

A case of significant hypoglycemia has been reported in a type II diabetic patient maintained on chlorpropamide (250 mg/day), after the addition of nortriptyline (125 mg/day).

Drugs Metabolized by P450 2D6 – The biochemical activity of the drug metabolizing isozyme cytochrome P450 2D6 (debrisoquin hydroxylase) is reduced in a subset of the Caucasian population (about 7% to 10% of Caucasians are so called “poor metabolizers”); reliable estimates of the prevalence of reduced P450 2D6 isozyme activity among Asian, African and other populations are not yet available. Poor metabolizers have higher than expected plasma concentrations of tricyclic antidepressants (TCAs) when given usual doses. Depending on the fraction of drug metabolized by P450 2D6, the increase in plasma concentration may be small, or quite large (8 fold increase in plasma AUC of the TCA).

In addition, certain drugs inhibit the activity of this isozyme and make normal metabolizers resemble poor metabolizers. An individual who is stable on a given dose of TCA may become abruptly toxic when given one of these inhibiting drugs as concomitant therapy. The drugs that inhibit cytochrome P450 2D6 include some that are not metabolized by the enzyme (quinidine; cimetidine) and many that are substrates for P450 2D6 (many other antidepressants, phenothiazines, and the Type 1C antiarrhythmics propafenone and flecainide). While all the selective serotonin reuptake inhibitors (SSRIs), e.g., fluoxetine, sertraline, and paroxetine, inhibit P450 2D6, they may vary in the extent of inhibition. The extent to which SSRI TCA interactions may pose clinical problems will depend on the degree of inhibition and the pharmacokinetics of the SSRI involved. Nevertheless, caution is indicated in the co-administration of TCAs with any of the SSRIs and also in switching from one class to the other. Of particular importance, sufficient time must elapse before initiating TCA treatment in a patient being withdrawn from fluoxetine, given the long half-life of the parent and active metabolite (at least 5 weeks may be necessary).

Concomitant use of tricyclic antidepressants with drugs that can inhibit cytochrome P450 2D6 may require lower doses than usually prescribed for either the tricyclic antidepressant or the other drug. Furthermore, whenever one of these other drugs is withdrawn from co-therapy, an increased dose of tricyclic antidepressant may be required. It is desirable to monitor TCA plasma levels whenever a TCA is going to be co-administered with another drug known to be an inhibitor of P450 2D6.

Monoamine Oxidase Inhibitors (MAOIs)

(See CONTRAINDICATIONS, WARNINGS, and DOSAGE AND ADMINISTRATION.)

Serotonergic Drugs

(See CONTRAINDICATIONS, WARNINGS, and DOSAGE AND ADMINISTRATION.)

Pediatric Use

Safety and effectiveness in the pediatric population have not been established (see BOX WARNING and WARNINGS, Clinical Worsening and Suicide Risk). Anyone considering the use of nortriptyline hydrochloride in a child or adolescent must balance the potential risks with the clinical need.

Geriatric Use

Clinical studies of Pamelor did not include sufficient numbers of subjects aged 65 and over to determine whether they respond differently from younger subjects. Other reported clinical experience indicates that, as with other tricyclic antidepressants, hepatic adverse events (characterized mainly by jaundice and elevated liver enzymes) are observed very rarely in geriatric patients and deaths associated with cholestatic liver damage have been reported in isolated instances. Cardiovascular function, particularly arrhythmias and fluctuations in blood pressure, should be monitored. There have also been reports of confusional states following tricyclic antidepressant administration in the elderly. Higher plasma concentrations of the active nortriptyline metabolite, 10-hydroxynortriptyline, have also been reported in elderly patients. As with other tricyclic antidepressants, dose selection for an elderly patient should usually be limited to the smallest effective total daily dose (see DOSAGE AND ADMINISTRATION).

ADVERSE REACTIONS

Note – Included in the following list are a few adverse reactions that have not been reported with this specific drug. However, the pharmacologic similarities among the tricyclic antidepressant drugs require that each of the reactions be considered when nortriptyline is administered.

Cardiovascular – Hypotension, hypertension, tachycardia, palpitation, myocardial infarction, arrhythmias, heart block, stroke.

Psychiatric – Confusional states (especially in the elderly) with hallucinations, disorientation, delusions; anxiety, restlessness, agitation; insomnia, panic, nightmares; hypomania; exacerbation of psychosis.

Neurologic – Numbness, tingling, paresthesias of extremities; incoordination, ataxia, tremors; peripheral neuropathy; extrapyramidal symptoms; seizures, alteration in EEG patterns; tinnitus.

Anticholinergic – Dry mouth and, rarely, associated sublingual adenitis; blurred vision, disturbance of accommodation, mydriasis; constipation, paralytic ileus; urinary retention, delayed micturition, dilation of the urinary tract.

Allergic – Skin rash, petechiae, urticaria, itching, photosensitization (avoid excessive exposure to sunlight); edema (general or of face and tongue), drug fever, cross-sensitivity with other tricyclic drugs.

Hematologic – Bone marrow depression, including agranulocytosis; eosinophilia; purpura; thrombocytopenia.

Gastrointestinal – Nausea and vomiting, anorexia, epigastric distress, diarrhea, peculiar taste, stomatitis, abdominal cramps, blacktongue.

Endocrine – Gynecomastia in the male, breast enlargement and galactorrhea in the female; increased or decreased libido, impotence; testicular swelling; elevation or depression of blood sugar levels; syndrome of inappropriate ADH (antidiuretic hormone) secretion.

Other – Jaundice (simulating obstructive), altered liver function; weight gain or loss; perspiration; flushing; urinary frequency, nocturia; drowsiness, dizziness, weakness, fatigue; headache; parotid swelling; alopecia.

Withdrawal Symptoms – Though these are not indicative of addiction, abrupt cessation of treatment after prolonged therapy may produce nausea, headache, and malaise.

Postmarketing Experience

The following adverse drug reaction has been reported during post-approval use of Pamelor. Because this reaction is reported voluntarily from a population of uncertain size, it is not always possible to reliably estimate frequency.

Cardiac Disorders – Brugada syndrome

Eye Disorders – angle-closure glaucoma

OVERDOSAGE

Deaths may occur from overdosage with this class of drugs. Multiple drug ingestion (including alcohol) is common in deliberate tricyclic antidepressant overdose. As the management is complex and changing, it is recommended that the physician contact a poison control center for current information on treatment. Signs and symptoms of toxicity develop rapidly after tricyclic antidepressant overdose, therefore, hospital monitoring is required as soon as possible.

Manifestations

Critical manifestations of overdose include: cardiac dysrhythmias, severe hypotension, shock, congestive heart failure, pulmonary edema, convulsions, and CNS depression, including coma. Changes in the electrocardiogram, particularly in QRS axis or width, are clinically significant indicators of tricyclic antidepressant toxicity.

Other signs of overdose may include: confusion, restlessness, disturbed concentration, transient visual hallucinations, dilated pupils, agitation, hyperactive reflexes, stupor, drowsiness, muscle rigidity, vomiting, hypothermia, hyperpyrexia, or any of the acute symptoms listed under ADVERSE REACTIONS. There have been reports of patients recovering from nortriptyline overdoses of up to 525 mg.

Management

General – Obtain an ECG and immediately initiate cardiac monitoring. Protect the patient's airway, establish an intravenous line and initiate gastric decontamination. A minimum of six hours of observation with cardiac monitoring and observation for signs of CNS or respiratory depression, hypotension, cardiac dysrhythmias and/or conduction blocks, and seizures is necessary. If signs of toxicity occur at any time during this period, extended monitoring is required. There are case reports of patients succumbing to fatal dysrhythmias late after overdose; these patients had clinical evidence of significant poisoning prior to death and most received inadequate gastrointestinal decontamination. Monitoring of plasma drug levels should not guide management of the patient.

Gastrointestinal Decontamination – All patients suspected of tricyclic antidepressant overdose should receive gastrointestinal decontamination. This should include large volume gastric lavage followed by activated charcoal. If consciousness is impaired, the airway should be secured prior to lavage. EMESIS IS CONTRAINDICATED.

Cardiovascular – A maximal limb-lead QRS duration of ≥0.10 seconds may be the best indication of the severity of the overdose. Intravenous sodium bicarbonate should be used to maintain the serum pH in the range of 7.45 to 7.55. If the pH response is inadequate, hyperventilation may also be used. Concomitant use of hyperventilation and sodium bicarbonate should be done with extreme caution, with frequent pH monitoring. A pH >7.60 or a pCO2 <20 mmHg is undesirable. Dysrhythmias unresponsive to sodium bicarbonate therapy/hyperventilation may respond to lidocaine, bretylium or phenytoin. Type 1A and 1C antiarrhythmics are generally contraindicated (e.g., quinidine, disopyramide, and procainamide). In rare instances, hemoperfusion may be beneficial in acute refractory cardiovascular instability in patients with acute toxicity. However, hemodialysis, peritoneal dialysis, exchange transfusions, and forced diuresis generally have been reported as ineffective in tricyclic antidepressant poisoning.

CNS – In patients with CNS depression, early intubation is advised because of the potential for abrupt deterioration. Seizures should be controlled with benzodiazepines, or if these are ineffective, other anticonvulsants (e.g., phenobarbital, phenytoin). Physostigmine is not recommended except to treat life-threatening symptoms that have been unresponsive to other therapies, and then only in consultation with a poison control center.

Psychiatric Follow-up – Since overdosage is often deliberate, patients may attempt suicide by other means during the recovery phase. Psychiatric referral may be appropriate.

Pediatric Management – The principles of management of child and adult overdosages are similar. It is strongly recommended that the physician contact the local poison control center for specific pediatric treatment.

DOSAGE AND ADMINISTRATION

Pamelor is not recommended for children.

Pamelor is administered orally in the form of capsules. Lower than usual dosages are recommended for elderly patients and adolescents. Lower dosages are also recommended for outpatients than for hospitalized patients who will be under close supervision. The physician should initiate dosage at a low level and increase it gradually, noting carefully the clinical response and any evidence of intolerance. Following remission, maintenance medication may be required for a longer period of time at the lowest dose that will maintain remission.

If a patient develops minor side effects, the dosage should be reduced. The drug should be discontinued promptly if adverse effects of a serious nature or allergic manifestations occur.

Usual Adult Dose – 25 mg three or four times daily; dosage should begin at a low level and be increased as required. As an alternate regimen, the total daily dosage may be given once a day. When doses above 100 mg daily are administered, plasma levels of nortriptyline should be monitored and maintained in the optimum range of 50 to 150 ng/mL. Doses above 150 mg/day are not recommended.

Elderly and Adolescent Patients – 30 to 50 mg/day, in divided doses, or the total daily dosage may be given once a day.

Switching a Patient To or From a Monoamine Oxidase Inhibitor (MAOI) Intended to Treat Psychiatric Disorders

At least 14 days should elapse between discontinuation of an MAOI intended to treat psychiatric disorders and initiation of therapy with Pamelor. Conversely, at least 14 days should be allowed after stopping Pamelor before starting an MAOI intended to treat psychiatric disorders (see CONTRAINDICATIONS).

Use of Pamelor With Other MAOIs, Such as Linezolid or Methylene Blue

Do not start Pamelor in a patient who is being treated with linezolid or intravenous methylene blue because there is increased risk of serotonin syndrome. In a patient who requires more urgent treatment of a psychiatric condition, other interventions, including hospitalization, should be considered (see CONTRAINDICATIONS).

In some cases, a patient already receiving Pamelor therapy may require urgent treatment with linezolid or intravenous methylene blue. If acceptable alternatives to linezolid or intravenous methylene blue treatment are not available and the potential benefits of linezolid or intravenous methylene blue treatment are judged to outweigh the risks of serotonin syndrome in a particular patient, Pamelor should be stopped promptly, and linezolid or intravenous methylene blue can be administered. The patient should be monitored for symptoms of serotonin syndrome for two weeks or until 24 hours after the last dose of linezolid or intravenous methylene blue, whichever comes first. Therapy with Pamelor may be resumed 24 hours after the last dose of linezolid or intravenous methylene blue (see WARNINGS).

The risk of administering methylene blue by non-intravenous routes (such as oral tablets or by local injection) or in intravenous doses much lower than 1 mg/kg with Pamelor is unclear. The clinician should, nevertheless, be aware of the possibility of emergent symptoms of serotonin syndrome with such use (see WARNINGS).

HOW SUPPLIED

Pamelor™ (nortriptyline HCl) Capsules USP

Pamelor™ (nortriptyline HCl) Capsules USP, equivalent to 10 mg, 25 mg, 50 mg, and 75 mg base, are available as follows:

10 mg: Light orange opaque cap printed “PAMELOR 10 mg” in black and white opaque body printed “” in black.

Bottles of 30..................NDC 0406-9910-03

25 mg: Light orange opaque cap printed “PAMELOR 25 mg” in black and white opaque body printed ““ in black.

Bottles of 30..................NDC 0406-9911-03

50 mg: White opaque cap printed “PAMELOR 50 mg” in black and white opaque body printed “” in black.

Bottles of 30..................NDC 0406-9912-03

75 mg: Light orange opaque cap printed “PAMELOR 75 mg” in black and light orange opaque body printed “” in black.

Bottles of 30..................NDC 0406-9913-03

Store and Dispense

Store at 20° to 25°C (68° to 77°F) [see USP Controlled Room Temperature].

Dispense in tight container (USP) with a child-resistant closure.

Mallinckrodt, the “M” brand mark, the Mallinckrodt Pharmaceuticals logo, and other brands are trademarks of a Mallinckrodt company.

© 2024 Mallinckrodt.

Product of Canada, Active Ingredient made in Ireland

Manufactured by:

Patheon Inc.
Whitby, Ontario, Canada
L1N 5Z5

Manufactured for:
SpecGx LLC
Webster Groves, MO 63119 USA

Rev 09/2024

Mallinckrodt™
Pharmaceuticals

Medication Guide – Pamelor™ (nortriptyline HCl) capsules USP

Antidepressant Medicines, Depression and other Serious Mental Illnesses, and Suicidal Thoughts or Actions

Read the Medication Guide that comes with you or your family member's antidepressant medicine. Talk to your, or your family member's, healthcare provider about:

- all risks and benefits of treatment with antidepressant medicines
- all treatment choices for depression or other serious mental illness

What is the most important information I should know about antidepressant medicines, depression and other serious mental illnesses, and suicidal thoughts or actions?

1. Antidepressant medicines may increase suicidal thoughts or actions in some children, teenagers, and young adults within the first few months of treatment.
2. Depression and other serious mental illnesses are the most important causes of suicidal thoughts and actions. Some people may have a particularly high risk of having suicidal thoughts or actions. These include people who have (or have a family history of) bipolar illness (also called manic-depressive illness) or suicidal thoughts or actions.
3. How can I watch for and try to prevent suicidal thoughts and actions in myself or a family member?
  - Pay close attention to any changes, especially sudden changes, in mood, behaviors, thoughts, or feelings. This is very important when an antidepressant medicine is started or when the dose is changed.
  - Call the healthcare provider right away to report new or sudden changes in mood, behavior, thoughts, or feelings.
  - Keep all follow-up visits with the healthcare provider as scheduled. Call the healthcare provider between visits as needed, especially if you have concerns about symptoms.

Call a healthcare provider right away if you or your family member has any of the following symptoms, especially if they are new, worse, or worry you:

- thoughts about suicide or dying
- attempts to commit suicide
- new or worse depression
- new or worse anxiety
- feeling very agitated or restless
- panic attacks
- trouble sleeping (insomnia)
- new or worse irritability
- acting aggressive, being angry, or violent
- acting on dangerous impulses
- an extreme increase in activity and talking (mania)
- other unusual changes in behavior or mood

Heart problem (Brugada Syndrome)

- If you have unexplained fainting or have a family history of sudden unexplained death before 45 years of age, you may have Brugada Syndrome and not know it.
- Talk to your healthcare provider right away if you faint or feel abnormal heartbeats.

Visual problems

- eye pain
- changes in vision
- swelling or redness in or around the eye

Only some people are at risk for these problems. You may want to undergo an eye examination to see if you are at risk and receive preventative treatment if you are.

Who should not take Pamelor?

Do not take Pamelor if you:

- take a monoamine oxidase inhibitor (MAOI). Ask your healthcare provider or pharmacist if you are not sure if you take an MAOI, including the antibiotic linezolid.
  - Do not take an MAOI within 2 weeks of stopping Pamelor unless directed to do so by your physician.
  - Do not start Pamelor if you stopped taking an MAOI in the last 2 weeks unless directed to do so by your physician.

What else do I need to know about antidepressant medicines?

- Never stop an antidepressant medicine without first talking to a healthcare provider. Stopping an antidepressant medicine suddenly can cause other symptoms.
- Antidepressants are medicines used to treat depression and other illnesses. It is important to discuss all the risks of treating depression and also the risks of not treating it. Patients and their families or other caregivers should discuss all treatment choices with the healthcare provider, not just the use of antidepressants.
- Antidepressant medicines have other side effects. Talk to the healthcare provider about the side effects of the medicine prescribed for you or your family member.
- Antidepressant medicines can interact with other medicines. Know all of the medicines that you or your family member takes. Keep a list of all medicines to show the healthcare provider. Do not start new medicines without first checking with your healthcare provider.
- Not all antidepressant medicines prescribed for children are FDA approved for use in children. Talk to your child's healthcare provider for more information.

Call your doctor for medical advice about side effects. You may report side effects to FDA at 1-800-FDA-1088.

This Medication Guide has been approved by the U.S. Food and Drug Administration.

© 2024 Mallinckrodt.

Product of Canada, Active Ingredient made in Ireland

Manufactured by:

Patheon Inc.
Whitby, Ontario, Canada
L1N 5Z5

Manufactured for:
SpecGx LLC
Webster Groves, MO 63119 USA

Mallinckrodt™

Rev 09/2024

PACKAGE LABEL - PRINCIPAL DISPLAY PANEL - 10 mg Bottle

NDC 0406-9910-03

30 Capsules

Pamelor™
(nortriptyline HCl) capsules USP

equivalent to
10 mg
base

Rx only

PHARMACIST: PLEASE DISPENSE WITH ATTACHED MEDICATION GUIDE

Mallinckrodt™

Rev 09/2024
2000017779

PACKAGE LABEL - PRINCIPAL DISPLAY PANEL - 25 mg Bottle

NDC 0406-9911-03

30 Capsules

Pamelor™
(nortriptyline HCl) capsules USP

equivalent to
25 mg
base

Rx only

PHARMACIST: PLEASE DISPENSE WITH ATTACHED MEDICATION GUIDE

Mallinckrodt™

Rev 09/2024
2000017780

PACKAGE LABEL - PRINCIPAL DISPLAY PANEL - 50 mg Bottle

NDC 0406-9912-03

30 Capsules

Pamelor™
(nortriptyline HCl) capsules USP

equivalent to
50 mg
base

Rx only

PHARMACIST: PLEASE DISPENSE WITH ATTACHED MEDICATION GUIDE

Mallinckrodt™

Rev 09/2024
2000017781

PACKAGE LABEL - PRINCIPAL DISPLAY PANEL - 75 mg Bottle

NDC 0406-9913-03

30 Capsules

Pamelor™
(nortriptyline HCl) capsules USP

equivalent to
75 mg
base

Rx only

PHARMACIST: PLEASE DISPENSE WITH ATTACHED MEDICATION GUIDE

Mallinckrodt™

Rev 09/2024
2000017782